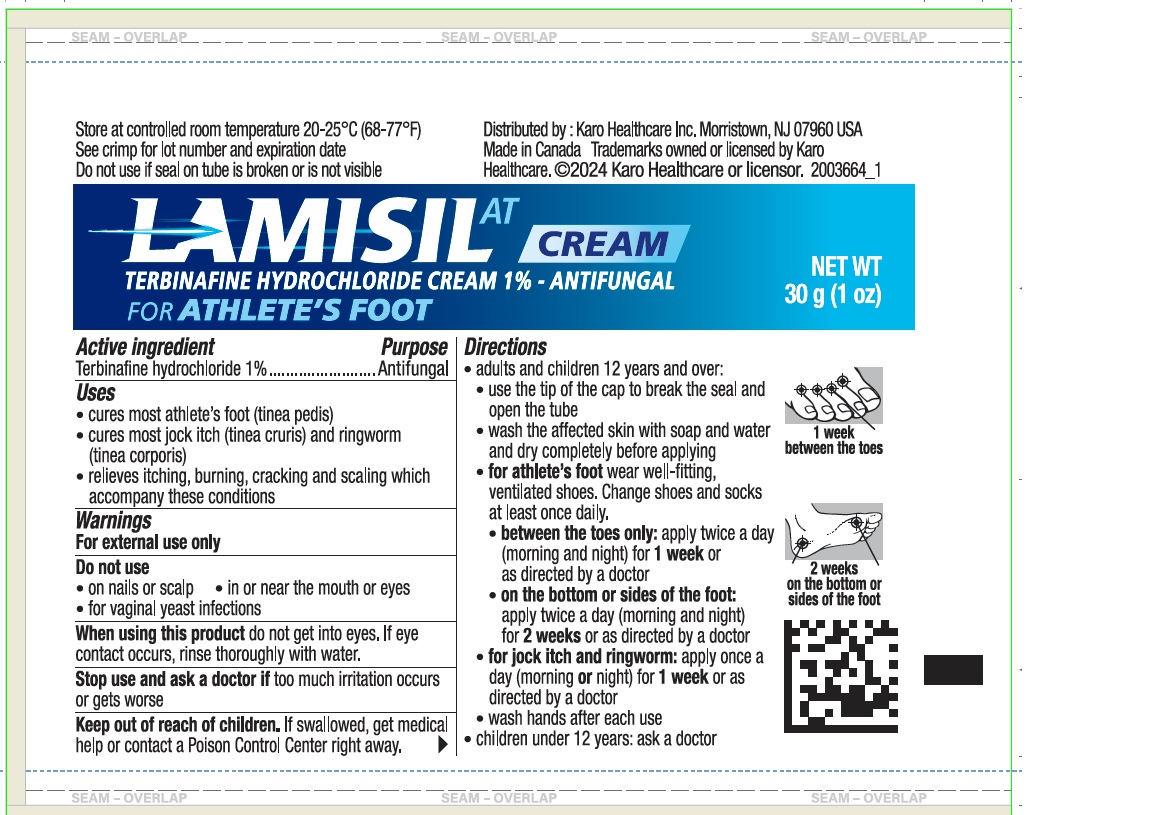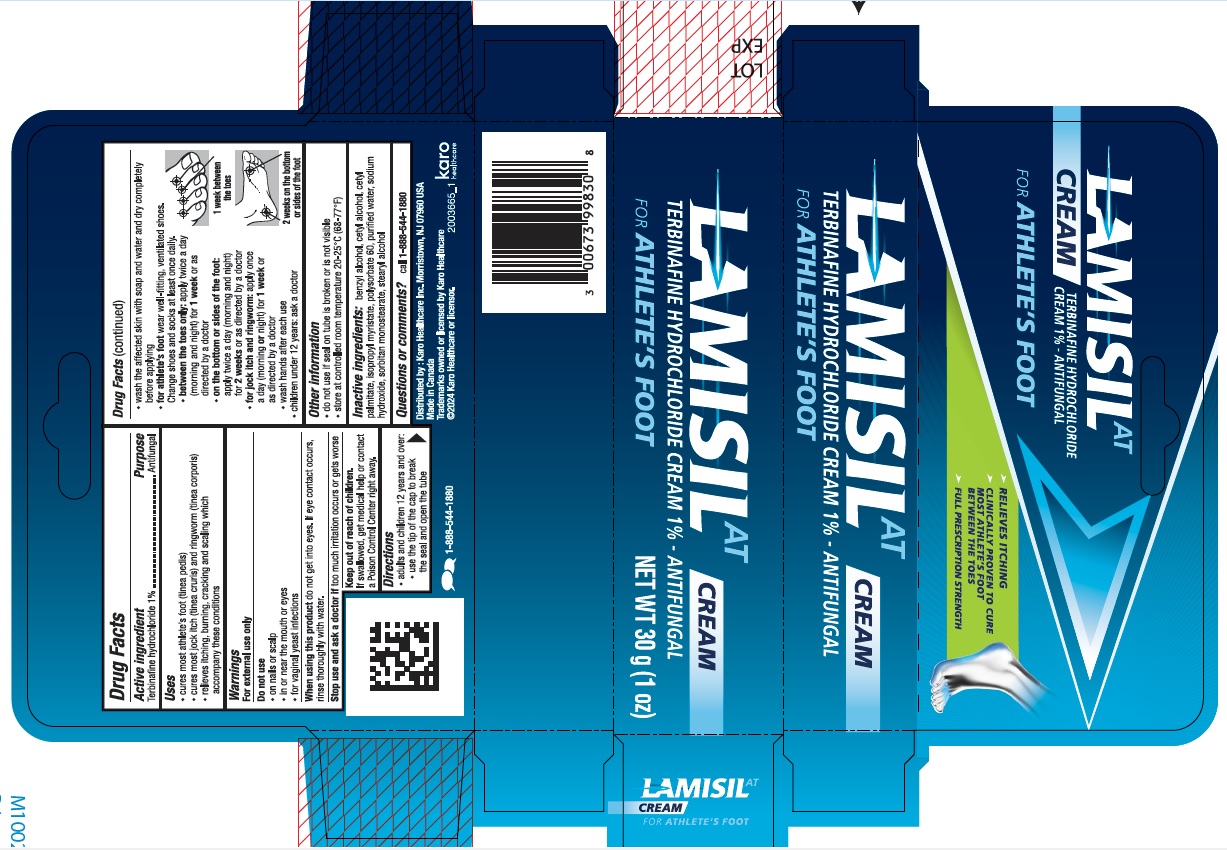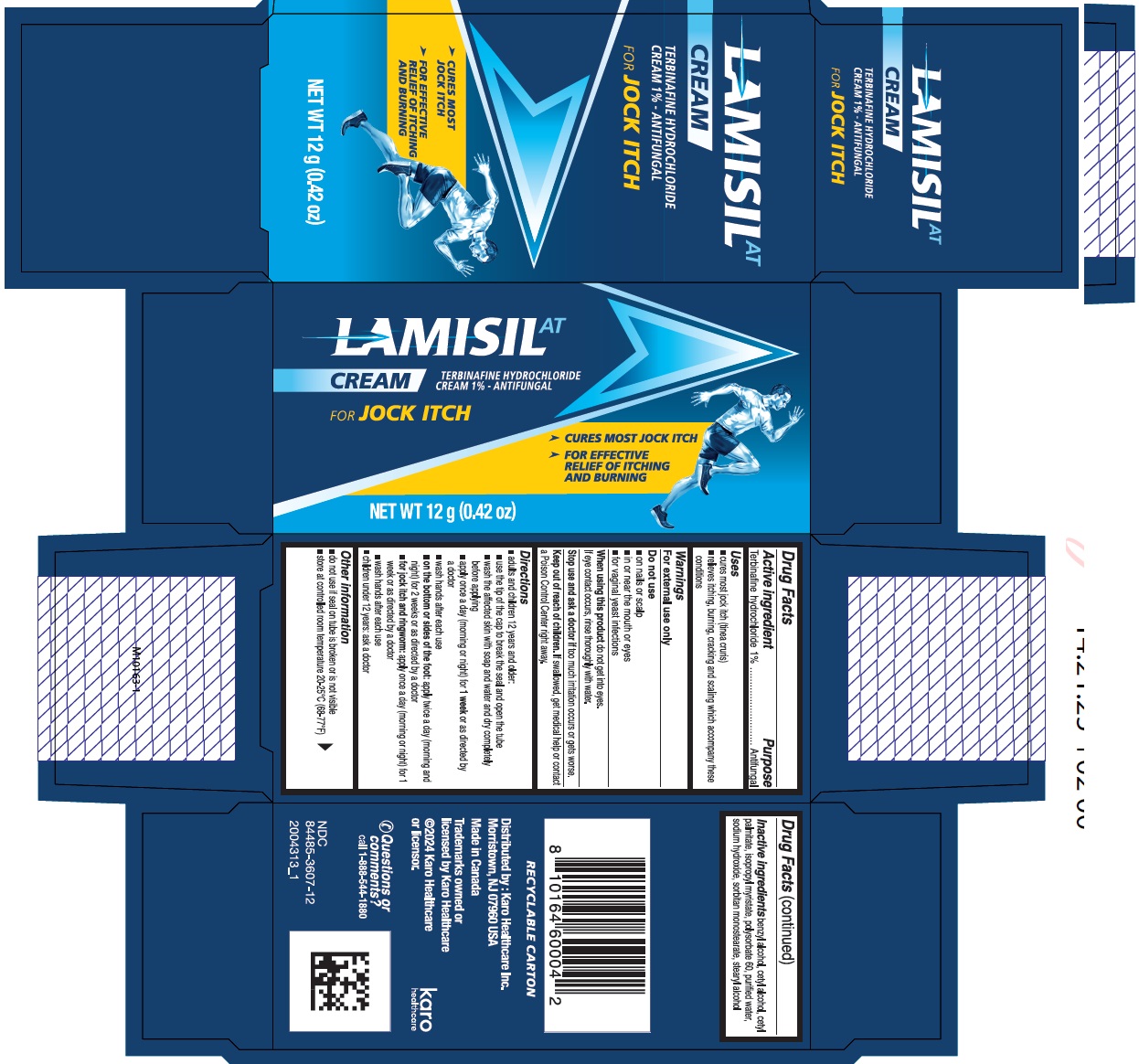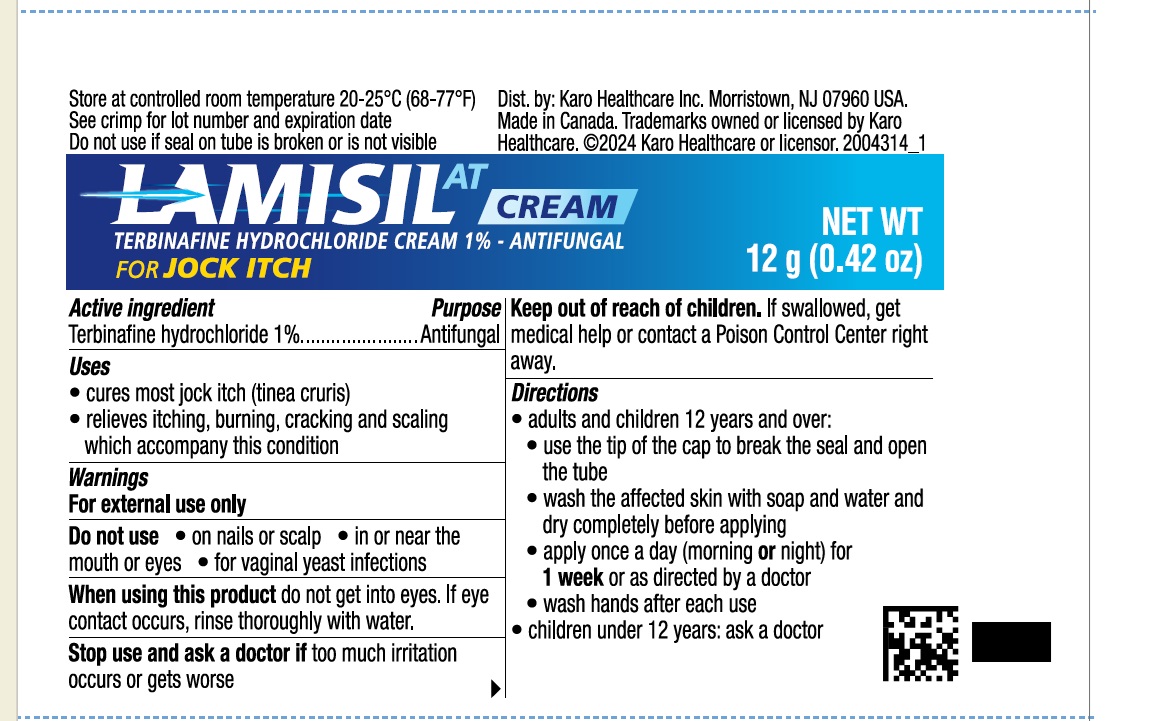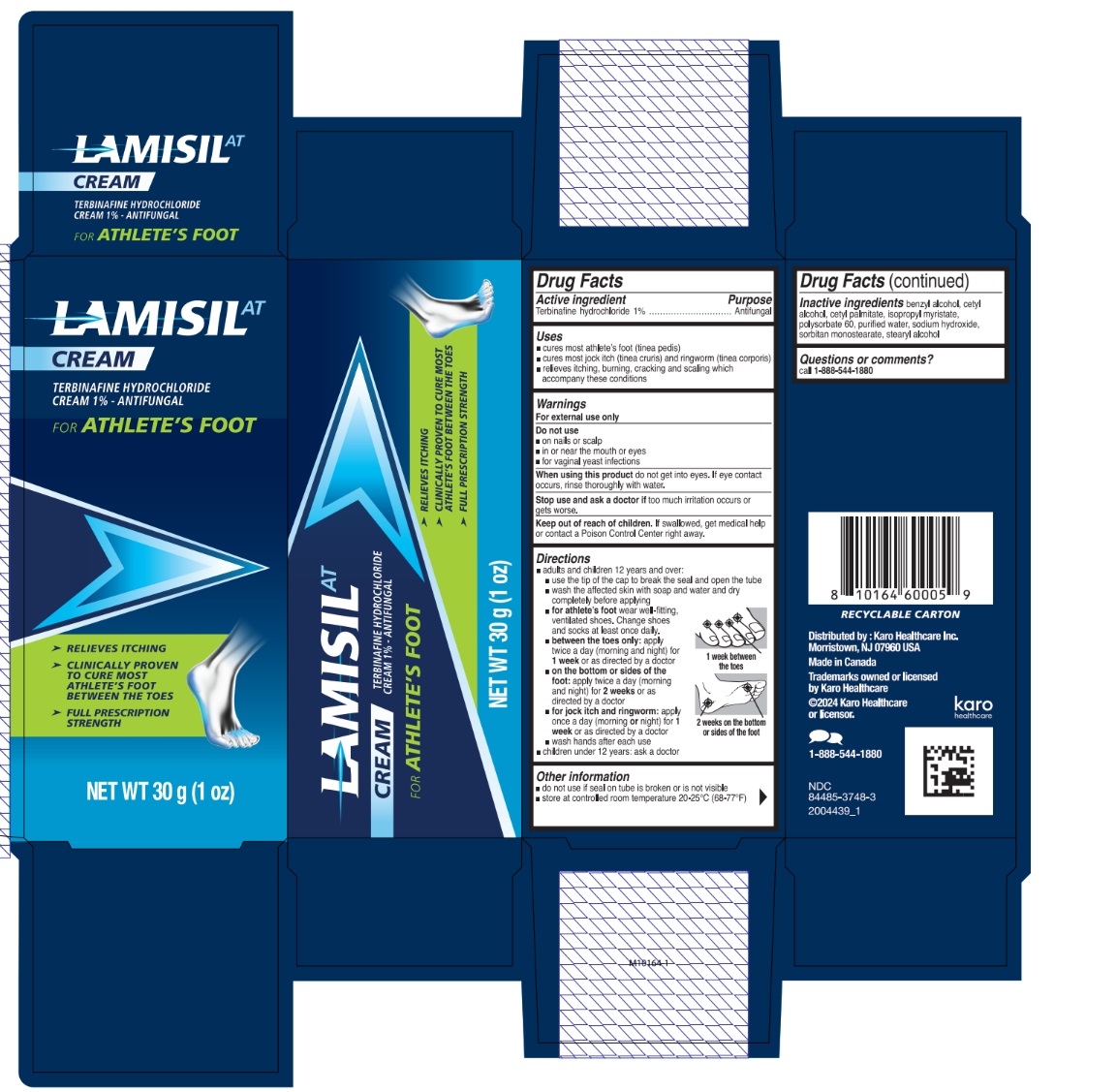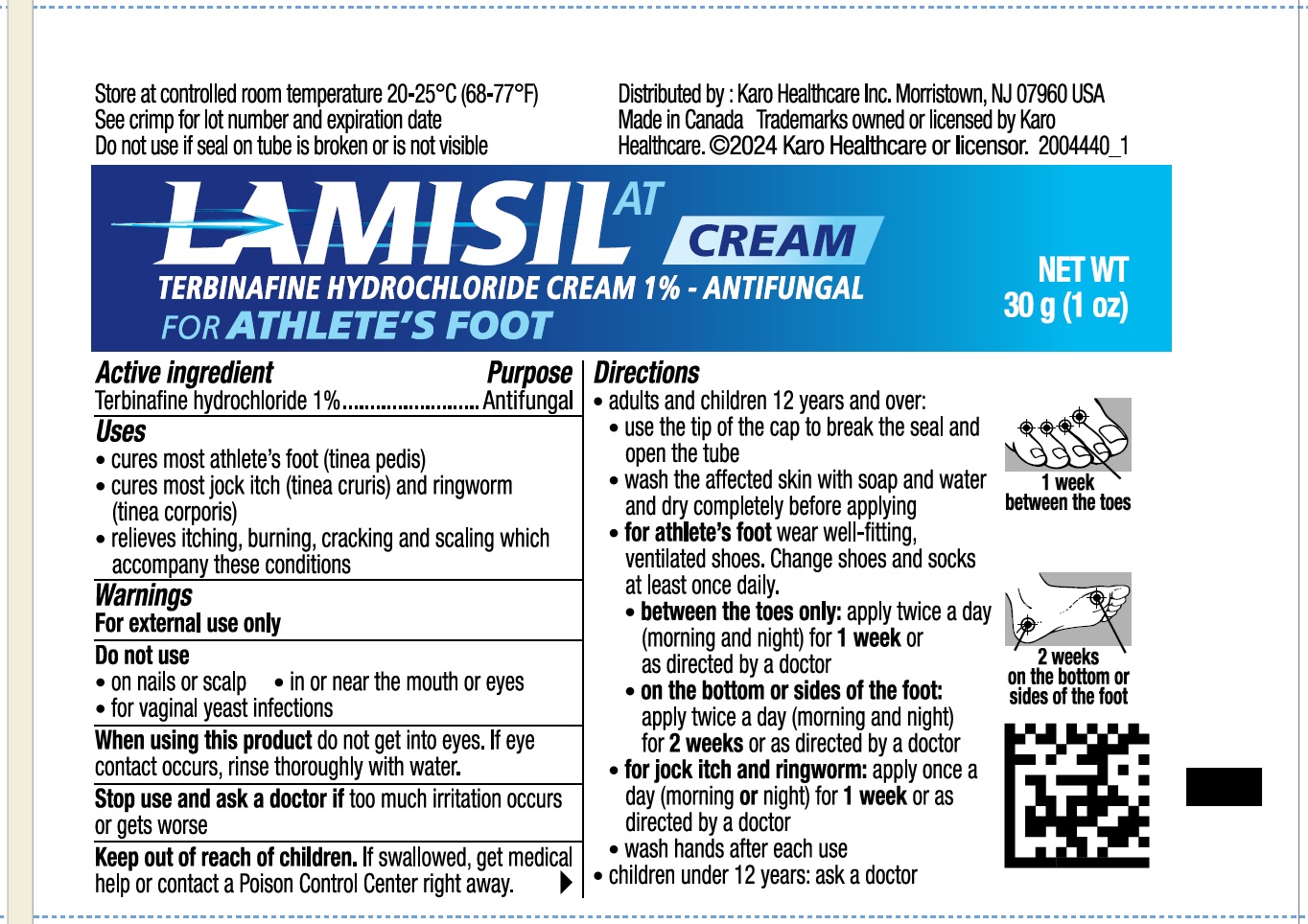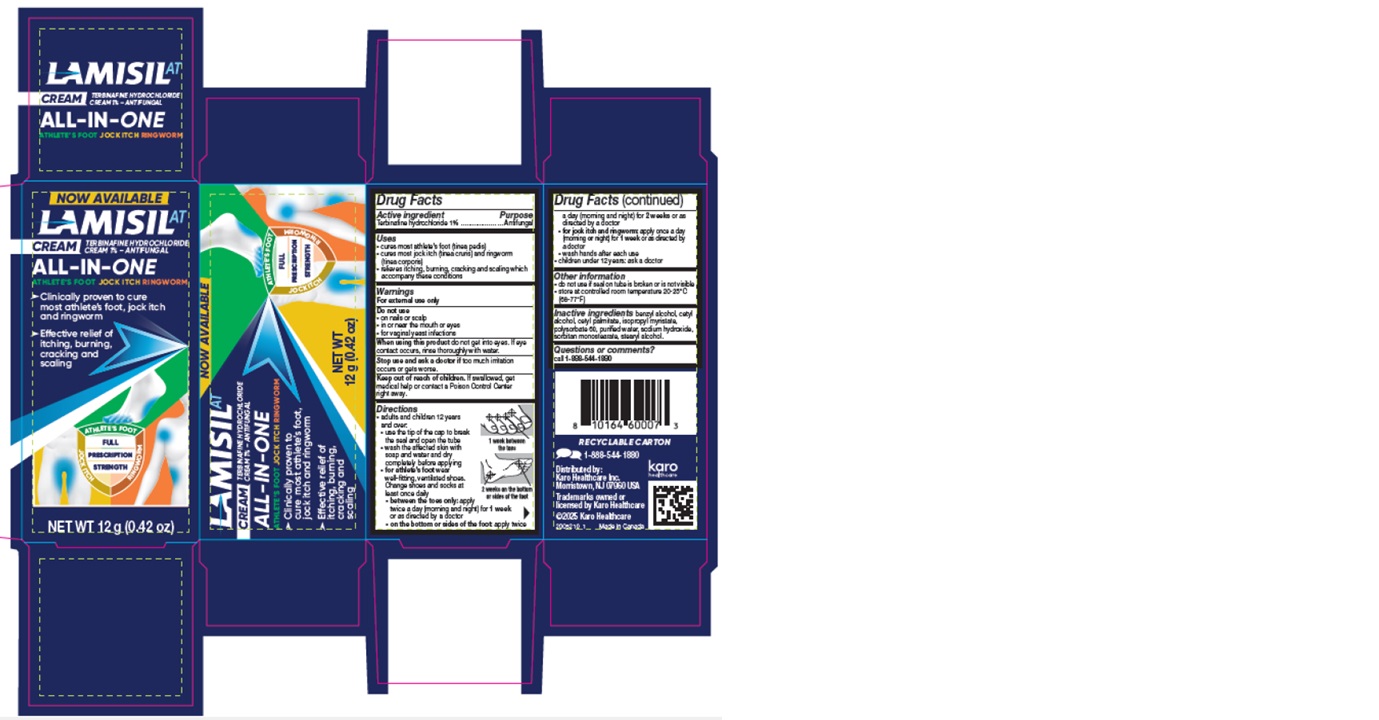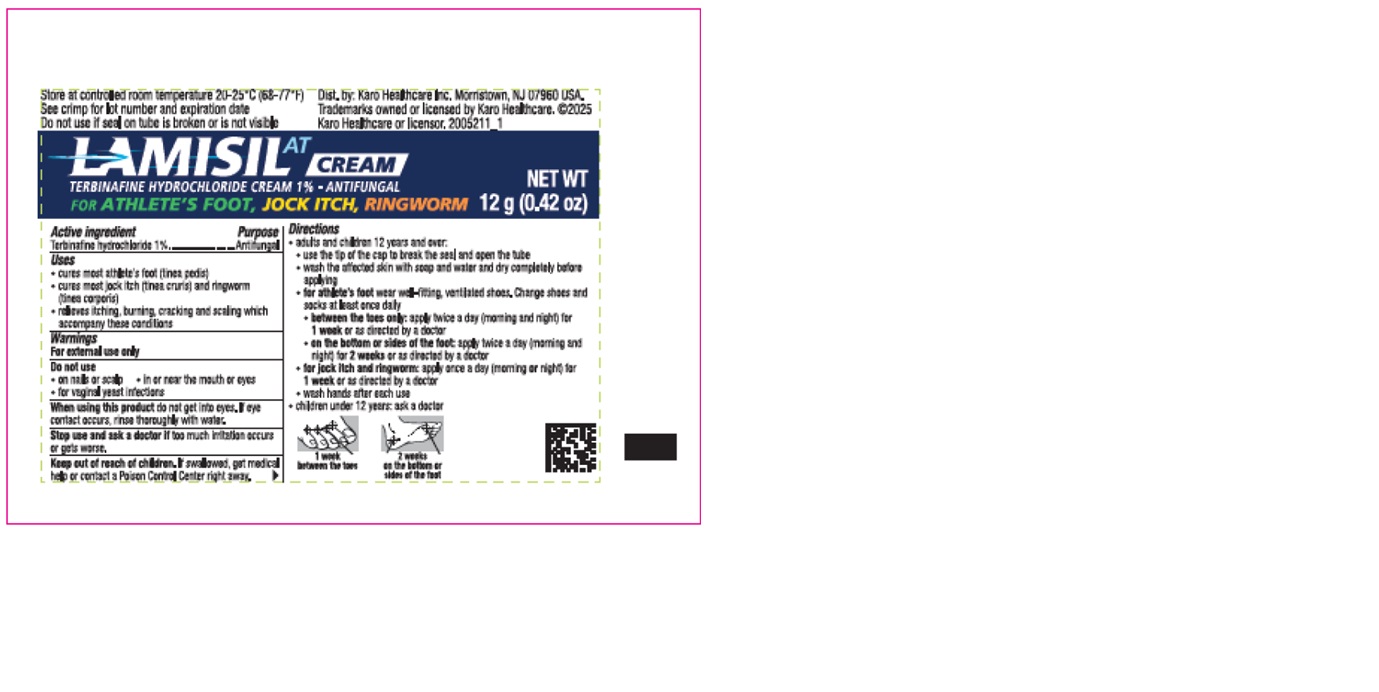 DRUG LABEL: LAMISIL AT TERBINAFINE HYDROCHLORIDE
NDC: 61047-139 | Form: CREAM
Manufacturer: Voyant Beauty, Inc.
Category: otc | Type: HUMAN OTC DRUG LABEL
Date: 20250917

ACTIVE INGREDIENTS: TERBINAFINE HYDROCHLORIDE 1 g/100 g
INACTIVE INGREDIENTS: SORBITAN MONOSTEARATE; BENZYL ALCOHOL; POLYSORBATE 60; STEARYL ALCOHOL; WATER; CETYL ALCOHOL; SODIUM HYDROXIDE; ISOPROPYL MYRISTATE; CETYL PALMITATE

Formula # 39900

ACTIVE INGREDIENT

Terbinafine hydrochloride 1%

PURPOSE

Antifungal

INDICATIONS AND USAGE

- cures most athlete's foot (tinea pedis)

- cure most jock itch (tinea cruris) and ringworm (tinea corporis)

- relieves itching, burning, cracking andf scaling which accompany this condition

WARNINGS

For external use only

DO NOT USE

- on nails or scalp

- in or near the mouth or eyes

- for vaginal yeast infections

WHEN USING

do not get into eyes. If eye contact occurs, rinse thoroughly with water

ask a doctor if too much irritation occurs or gets worse

KEEP OUT OF REACH OF CHILDREN

If swallowed, get medical help or contact a Poison Control Center right away.

Directions

- adults and children 12 years and over:

- use the tip of the cap to break the seal and open the tube
- wash the affected skin with soap and water and dry completely before applying
- for athlete's foot wear well-fitting, ventilated shoes. Change shoes and socks at least once daily.
- between the toes only: apply twice a day (morning and night) for 1 week or as directed by a doctor
- on the bottom or sides of the foot: apply twice a day (morning and night) for 2 weeks or as directed by a doctor
- for jock itch and ringworm: apply once a day (morning or night) for 1 week or as directed by a doctor
- wash hands after each use

- children under 12 years: ask a doctor

Other Information

- do no use if seal on tube is broken or is not visible

- store at controlled room temperature 20-25C (68-77F)

INACTIVE INGREDIENT

benzyl alcohol, cetyl alcohol, cetyl palmitate, isopropyl myristate, polysorbate 60, purified water, sodium hydroxide, sorbitan monostearate, stearly alcohol

QUESTIONS

call 1-888-544-1880

30g (1oz)

Lamisil AT

Cream

Terbinafine Hydrochloride

Cream 1% - Antifungal

For Athlete's Foot

Relieves Itching

Clinically Proven

to cure most

athelete's foot

between the toes

Fill prescription

strength

NET WT 30 g (1 oz)

12g (0.42oz)

LAMISIL AT

CREAM

TERBINAFINE HYDROCHLORIDE

CREAM 1% - ANTIFUNGAL

FOR JOCK ITCH

CURES MOST

JOCK ITCH

FOR EFFECTIVE

REFLIEF OF ITCHING

AND BURNING

NEW WT 12G (0.42OZ)

12g new graphics

NOW AVAILABEL

LAMISIL AT

CREAM

TERBINAFINE HYDROCHLORIDE CREAM 1% - ANTIFUNGAL

ALL-IN-ONE

Athlete's Foot - Jock Itch - Ringworm

Clinically proven to cure most athlete's foot, jock itch, and ringworm

Effective relief of itching, burning, cracking and scaling

Full Prescription Strength

Net wt 12g (0.42oz)